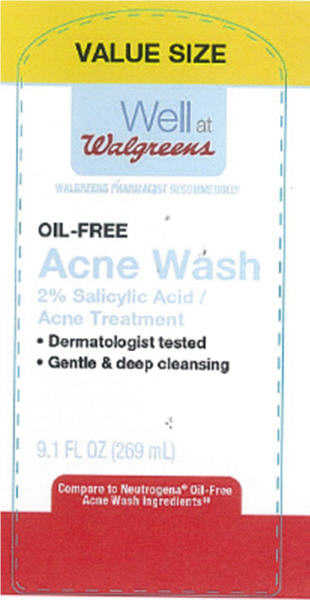 DRUG LABEL: Walgreens Oil-Free Acne Wash
NDC: 0363-0536 | Form: SOLUTION
Manufacturer: Walgreens Company
Category: otc | Type: HUMAN OTC DRUG LABEL
Date: 20140110

ACTIVE INGREDIENTS: SALICYLIC ACID 2 g/100 mL
INACTIVE INGREDIENTS: SODIUM C14-16 OLEFIN SULFONATE; WATER; COCAMIDOPROPYL BETAINE; PROPYLENE GLYCOL; SORBITAN MONOLAURATE; C12-15 ALKYL LACTATE; FD&C YELLOW NO. 5; COCAMIDOPROPYL PG-DIMONIUM CHLORIDE PHOSPHATE; BENZALKONIUM CHLORIDE; CHAMOMILE; ALOE VERA LEAF; EDETATE DISODIUM; FD&C RED NO. 40

Well at Walgreens Oil-Free Acne Wash

Active ingredient

Salicylic Acid 2.0%

Purpose

Acne Treatment

Indications

- for the treatment of acne

Warnings

For external use only.

Using other topical acne medications at the same time or immediately following use of this product may increase dryness or irritation of the skin. If this occurs, only one medication should be used unless directed by a doctor.

Keep Out of Reach of Children.

If swallowed, get medical help or contact a Poison Control Center right away. Avoid contact with eyes. If contact occurs, flush thoroughly with water.

Directions

- Clean twice daily
- Gently massage onto wet face, add water and work into a lather
- Rinse thoroughly

Other Information

- protect the product in this container from excessive heat and direct sun

Inactive ingredients

sodium C14-16 olefin sulfonate, water, cocamidopropyl betaine, propylene glycol, fragrance, PEG-80 sorbitan laurate, C12-15 alkyl lactate, yellow 5, cocamidopropyl PG-dimonium chloride phosphate, benzalkonium chloride, chamomilla recutita (matricaria) flower extract, aloe barbadensis leaf juice, disodium EDTA, red 40

Distributed by: Walgreen Co.
200 Wilmot Rd., Deerfield, IL 60015
100% Satisfaction Guaranteed

walgreens.com
©2012 Walgreen Co.

Manufactured in Israel

Package/Label Principal Display Panel

Well at Walgreens
Walgreens Pharmacist Recommended
Oil-Free Acne Wash
2% Salicylic Acid / Acne Treatment

- Dermatologist tested
- Gentle & deep cleansing

9.1 Fl Oz (269 mL)

Compare to Neutrogena® Oil-Free Acne Wash Ingredient

Carton Label